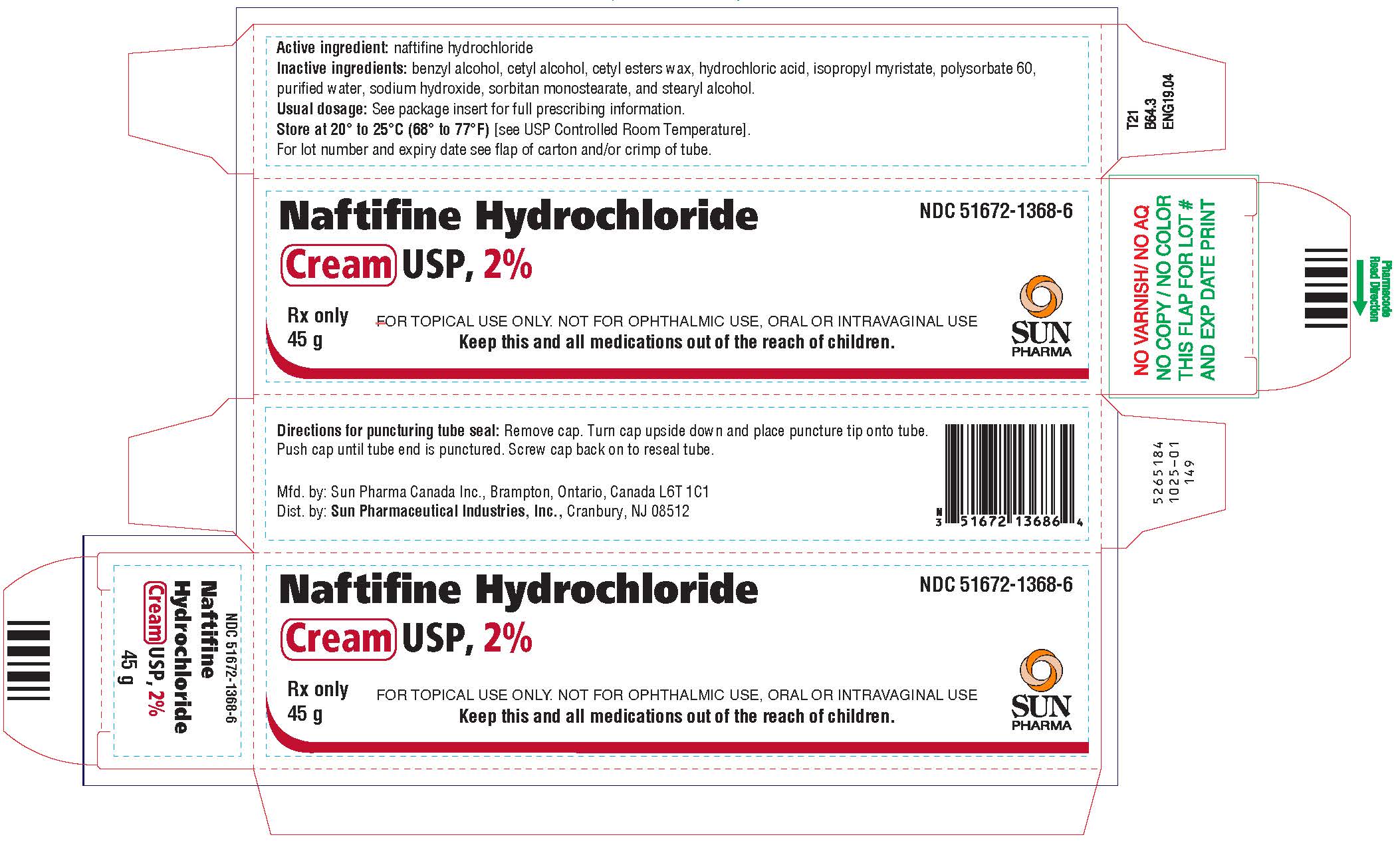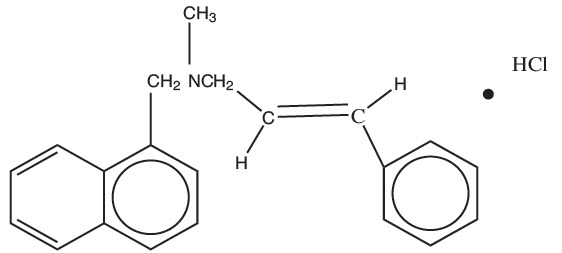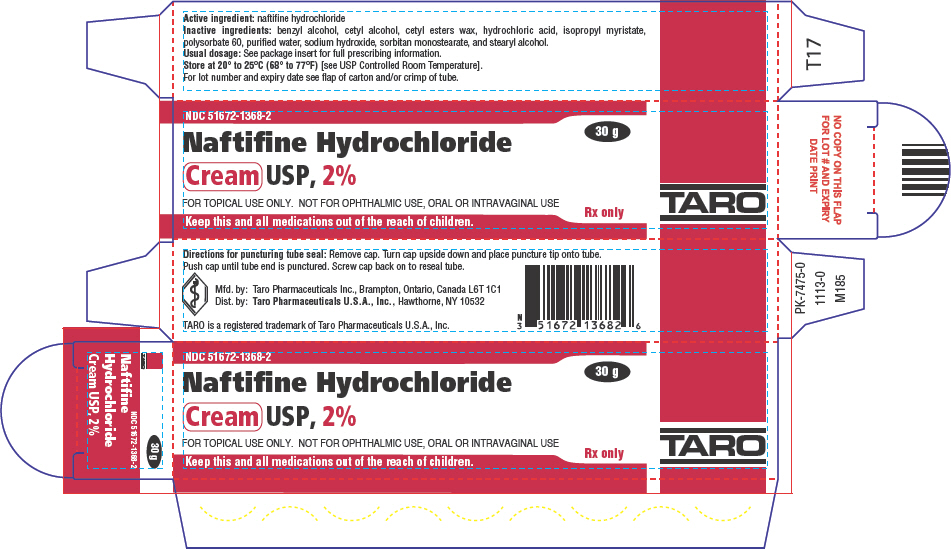 DRUG LABEL: Naftifine Hydrochloride
NDC: 51672-1368 | Form: CREAM
Manufacturer: Sun Pharmaceutical Industries, Inc.
Category: prescription | Type: HUMAN PRESCRIPTION DRUG LABEL
Date: 20251114

ACTIVE INGREDIENTS: NAFTIFINE HYDROCHLORIDE 20 mg/1 g
INACTIVE INGREDIENTS: BENZYL ALCOHOL; CETYL ALCOHOL; CETYL ESTERS WAX; ISOPROPYL MYRISTATE; POLYSORBATE 60; SODIUM HYDROXIDE; WATER; SORBITAN MONOSTEARATE; STEARYL ALCOHOL; HYDROCHLORIC ACID

HIGHLIGHTS OF PRESCRIBING INFORMATION

These highlights do not include all the information needed to use NAFTIFINE HYDROCHLORIDE CREAM safely and effectively. See full prescribing information for NAFTIFINE HYDROCHLORIDE CREAM
NAFTIFINE HYDROCHLORIDE cream, for topical use
Initial U.S. Approval: 1988

1 INDICATIONS AND USAGE

Naftifine Hydrochloride Cream is an allylamine antifungal indicated for the treatment of interdigital tinea pedis, tinea cruris, and tinea corporis caused by the organism Trichophyton rubrum.

2 DOSAGE AND ADMINISTRATION

For topical use only. Naftifine Hydrochloride Cream is not for ophthalmic, oral, or intravaginal use. (2)

Apply a thin layer of Naftifine Hydrochloride Cream once-daily to the affected areas plus a ½ inch margin of healthy surrounding skin for 2 weeks. (2)

3 DOSAGE FORMS AND STRENGTHS

Cream: 2%

4 CONTRAINDICATIONS

None

5 WARNINGS AND PRECAUTIONS

Discontinue treatment if redness or irritation develops with Naftifine Hydrochloride Cream use. (5.1)

6 ADVERSE REACTIONS

The most common adverse reaction (≥1%) is pruritus. (6.1)

To report SUSPECTED ADVERSE REACTIONS, contact Sun Pharmaceutical Industries, Inc., at 1-866-923-4914 or FDA at 1-800-FDA-1088 or www.fda.gov/medwatch.

FULL PRESCRIBING INFORMATION

1 INDICATIONS AND USAGE

Naftifine Hydrochloride Cream is indicated for the treatment of interdigital tinea pedis, tinea cruris, and tinea corporis caused by the organism Trichophyton rubrum.

2 DOSAGE AND ADMINISTRATION

For topical use only. Naftifine Hydrochloride Cream is not for ophthalmic, oral, or intravaginal use. Apply a thin layer of Naftifine Hydrochloride Cream once-daily to the affected areas plus a ½ inch margin of healthy surrounding skin for 2 weeks.

3 DOSAGE FORMS AND STRENGTHS

Each gram of Naftifine Hydrochloride Cream contains 20 mg of naftifine hydrochloride (2%) in a white to off-white base.

4 CONTRAINDICATIONS

None

5 WARNINGS AND PRECAUTIONS

5.1 Local Adverse Reactions

Discontinue treatment if irritation or sensitivity develops with the use of Naftifine Hydrochloride Cream. Direct patients to contact their physician if these conditions develop following use of Naftifine Hydrochloride Cream.

6 ADVERSE REACTIONS

6.1 Clinical Trials Experience

Because clinical trials are conducted under widely varying conditions, adverse reaction rates observed in the clinical trials of a drug cannot be directly compared to rates in the clinical trials of another drug and may not reflect the rates observed in clinical practice.

During clinical trials, 903 subjects were exposed to naftifine 1% and 2% cream formulations. A total of 564 subjects with interdigital tinea pedis, tinea cruris, or tinea corporis were treated with Naftifine Hydrochloride Cream.

In two randomized, vehicle-controlled trials (400 subjects were treated with Naftifine Hydrochloride Cream). The population was 12 to 88 years old, primarily male (79%), 48% Caucasian, 36% Black or African American, 40% Hispanic or Latino and had either predominantly interdigital tinea pedis or tinea cruris. Most subjects received doses once-daily, topically, for 2 weeks to cover the affected skin areas plus a ½ inch margin of surrounding healthy skin. In the two vehicle-controlled trials, 17.5% of Naftifine Hydrochloride Cream treated subjects experienced an adverse reaction compared with 19.3% of vehicle subjects. The most common adverse reaction (≥1%) is pruritus. Most adverse reactions were mild in severity. The incidence of adverse reactions in the Naftifine Hydrochloride Cream treated population was not significantly different than in the vehicle treated population.

In a third randomized, vehicle-controlled trial, 116 pediatric subjects with tinea corporis were treated with Naftifine Hydrochloride Cream. The population was aged ≥2 to <18 years (mean age of 9 years), predominately male (61%), 47% White, 51% Black or African American, 92% Hispanic or Latino, and infected with tinea corporis. Naftifine Hydrochloride Cream was topically applied once daily for 2 weeks to all affected body surface areas with tinea corporis plus a ½ inch margin of healthy skin surrounding the affected lesions. The incidence of adverse reactions in the Naftifine Hydrochloride Cream treated population was not significantly different than in the vehicle treated population.

In two open-label pediatric pharmacokinetics and safety trials, 49 pediatric subjects 2 to <18 years of age with interdigital tinea pedis, tinea cruris, and tinea corporis received Naftifine Hydrochloride Cream. The incidence of adverse reactions in the pediatric population was similar to that observed in the adult population.

6.2 Postmarketing Experience

The following adverse reactions have been identified during post-approval use of naftifine hydrochloride: redness/irritation, inflammation, maceration, swelling, burning, blisters, serous drainage, crusting, headache, dizziness, leukopenia, agranulocytosis.

Because these reactions are reported voluntarily from a population of uncertain size, it is not always possible to reliably estimate their frequency or establish a causal relationship to drug exposure.

8 USE IN SPECIFIC POPULATIONS

8.1 Pregnancy

Risk Summary

There are no available data with Naftifine Hydrochloride Cream in pregnant women to inform the drug-associated risk for major birth defects and miscarriage. In animal reproduction studies, no adverse effects on embryofetal development were seen at oral doses administered during the period of organogenesis up to 18 times the maximum recommended human dose (MRHD) in pregnant rats or subcutaneous doses administered during the period of organogenesis up to 2 times the MRHD in pregnant rats or 4 times the MRHD in pregnant rabbits [see Data] .

The estimated background risk of major birth defects and miscarriage for the indicated population is unknown. All pregnancies have a background risk of birth defect, loss, or other adverse outcomes. In the U.S. general population, the estimated background risk of major birth defects and miscarriage in clinically recognized pregnancies is 2 to 4% and 15 to 20%, respectively.

Data

Animal Data

Systemic embryofetal development studies were conducted in rats and rabbits. For the comparison of animal to human doses based on body surface area comparison (mg/m^2), the MRHD is set at 8 g 2% cream per day (2.67 mg/kg/day for a 60 kg individual).

Oral doses of 30 mg/kg/day, 100 mg/kg/day and 300 mg/kg/day naftifine hydrochloride were administered during the period of organogenesis to pregnant female rats. No treatment-related effects on embryofetal development were noted at doses up to 300 mg/kg/day (18 times MRHD). Subcutaneous doses of 10 mg/kg/day and 30 mg/kg/day naftifine hydrochloride were administered during the period of organogenesis to pregnant female rats. No treatment-related effects on embryofetal development were noted at 30 mg/kg/day (2 times MRHD). Subcutaneous doses of 3 mg/kg/day, 10 mg/kg/day and 30 mg/kg/day naftifine hydrochloride were administered during the period of organogenesis to pregnant female rabbits. No treatment-related effects on embryofetal development were noted at 30 mg/kg/day (4 times MRHD).

A peri- and post-natal development study was conducted in rats. Oral doses of 30 mg/kg/day, 100 mg/kg/day and 300 mg/kg/day naftifine hydrochloride were administered to female rats from gestational day 14 to lactation day 21. Reduced body weight gain of females during gestation and of the offspring during lactation was noted at 300 mg/kg/day (18 times MRHD). No developmental toxicity was noted at 100 mg/kg/day (6 times MRHD).

8.2 Lactation

Risk Summary

There is no information available on the presence of Naftifine Hydrochloride Cream in human milk, the effects of the drug on the breastfed infant, or the effects of the drug on milk production. The lack of clinical data during lactation precludes a clear determination of the risk of Naftifine Hydrochloride Cream to an infant during lactation; therefore, the development and health benefits of breastfeeding should be considered along with the mother's clinical need for Naftifine Hydrochloride Cream and any potential adverse effects on the breastfed infant from Naftifine Hydrochloride Cream or from the underlying maternal condition.

8.4 Pediatric Use

The safety and effectiveness of Naftifine Hydrochloride Cream have been established in pediatric patients age 12 and above with interdigital tinea pedis and tinea cruris and age 2 and above with tinea corporis [see Clinical Studies (14)and Clinical Pharmacology (12.3)] .

Use of Naftifine Hydrochloride Cream in these age groups is supported by evidence from adequate and well controlled studies in adults and children, with additional safety and PK data from two open label trials conducted in 49 pediatric subjects exposed to Naftifine Hydrochloride Cream [see Clinical Studies (14)and Clinical Pharmacology (12.3)] .

Safety and effectiveness of Naftifine Hydrochloride Cream in the treatment of tinea cruris and interdigital tinea pedis in pediatric patients less than 12 years of age have not been established. Safety and effectiveness of Naftifine Hydrochloride Cream in the treatment of tinea corporis in pediatric patients less than 2 years of age have not been established.

8.5 Geriatric Use

Clinical studies of Naftifine Hydrochloride Cream did not include sufficient numbers of subjects aged 65 and over to determine whether they respond differently from younger subjects.

11 DESCRIPTION

Naftifine Hydrochloride Cream is a white to off-white cream for topical use only. Each gram of Naftifine Hydrochloride Cream contains 20 mg of naftifine hydrochloride (2%), a synthetic allylamine antifungal compound.

Chemically, naftifine HCl is (E)-N-Cinnamyl-N-methyl-1-napthalenemethylamine hydrochloride.

The molecular formula is C21H21N∙HCl with a molecular weight of 323.86.

The structural formula of naftifine hydrochloride is:

Naftifine Hydrochloride Cream contains the following inactive ingredients: benzyl alcohol, cetyl alcohol, cetyl esters wax, hydrochloric acid, isopropyl myristate, polysorbate 60, purified water, sodium hydroxide, sorbitan monostearate, and stearyl alcohol.

12 CLINICAL PHARMACOLOGY

12.1 Mechanism of Action

Naftifine Hydrochloride Cream is a topical antifungal drug [see Clinical Pharmacology (12.4)]

12.2 Pharmacodynamics

The pharmacodynamics of Naftifine Hydrochloride Cream have not been established.

12.3 Pharmacokinetics

In vitroand in vivobioavailability studies have demonstrated that naftifine penetrates the stratum corneum in sufficient concentration to inhibit the growth of dermatophytes.

The pharmacokinetics of Naftifine Hydrochloride Cream was evaluated following once-daily topical application for 2 weeks to 21 adult subjects, both males and females, with both tinea pedis and tinea cruris. The median total amount of cream applied was 6.4 g (range 5.3 to 7.5 g) per day. The results showed that the systemic exposure (i.e., maximum concentration (Cmax) and area under the curve from time 0 to 24 hours (AUC0-24)) to naftifine increased over the 2 week treatment period in all the 21 subjects. Geometric mean (coefficient of variation or CV%) AUC0-24was 117 (41.2) ng*hr/mL on Day 1, and 204 (28.5) ng*hr/mL on Day 14. Geometric mean (CV%) Cmaxwas 7 ng/mL (55.6) on Day 1 and 11 ng/mL (29.3) on Day 14. Median time to Cmax(Tmax) was 8 hours (range: 4 to 24 hours) on Day 1 and 6 hours (range: 0 to 16 hours) on Day 14. Accumulation after 14 days of topical application was less than two fold. Trough concentrations generally increased throughout the 14 day study period. Naftifine continued to be detected in plasma in 13/21 (62%) subjects on Day 28, the mean (standard deviation or SD) plasma concentrations were 1.6 ± 0.5 ng/mL (range below limit of quantitation (BLQ) to 3 ng/mL). In the same pharmacokinetic trial conducted in patients with tinea pedis and tinea cruris, median fraction of the dose excreted in urine during the treatment period was 0.0016% on Day 1 versus 0.0020% on Day 14.

In a second trial that enrolled 22 subjects, the pharmacokinetics of Naftifine Hydrochloride Cream was evaluated in 20 pediatric subjects 13 to <18 years of age with both tinea pedis and tinea cruris. Subjects were treated with a median dose of 8.1 g (range 6.6 to 10.1 g) applied to the affected areas once daily for 2 weeks. The results showed that the systemic exposure increased over the treatment period. Geometric mean (CV%) AUC0-24was 138 (50.2) ng*hr/mL on Day 1, and 192 (74.9) ng*hr/mL on Day 14. Geometric mean (CV%) Cmaxwas 9.21 ng/mL (48.4) on Day 1 and 12.7 ng/mL (67.2) on Day 14. Median fraction of the dose excreted in urine during the treatment period was 0.0030% on Day 1 and 0.0033% on Day 14.

A third trial evaluated the pharmacokinetics of Naftifine Hydrochloride Cream in 27 pediatric subjects 2 to < 12 years of age with at least moderate tinea corporis. Subjects were divided into younger (ages 2 to < 6 years, 17 subjects) and older (6 to <12 years, 10 subjects) groups. Median doses of 1.3 g (range 1 to 3.1 g) and 2.3 g (range 2.2 to 4.2 g) were applied once-daily for 2 weeks in the younger and older groups, respectively, to the affected area plus a ½ inch margin. Plasma and urine pharmacokinetic assessments were conducted on Day 1 in the older group only and on Day 14 in both groups. All subjects showed measurable levels of naftifine in plasma after topical application of Naftifine Hydrochloride Cream. Following a single dose on Day 1 in subjects 6 to < 12 years of age, the geometric mean (CV%) values of Cmaxand AUC0-24were 3.60 (76.6) ng/mL and 49.8 (64.4) ng*h/mL, respectively. On Day 14 in this group, the Cmaxand AUC0-24were 3.31 (51.2) ng/mL and 52.4 (49.2) ng*h/mL, respectively. In subjects 2 to < 6 years of age on Day 14, the Cmaxand AUC0-24were 3.98 (186) ng/mL and 54.8 (150) ng*h/mL, respectively. In the older group of subjects 6 to 12 years of age, the systemic exposures (both Cmaxand AUC0-24) on Days 1 and 14 were comparable. The median fraction of the dose excreted into urine over 24 hours following drug applications on Day 1 and Day 14 was 0.0029% and 0.0014%, respectively.

12.4 Microbiology

Although the exact mechanism of action against fungi is not known, naftifine hydrochloride appears to interfere with sterol biosynthesis by inhibiting the enzyme squalene 2, 3-epoxidase.This inhibition of enzyme activity results in decreased amounts of sterols, especially ergosterol, and a corresponding accumulation of squalene in the cells.

Mechanism of Resistance

To date, a mechanism of resistance to naftifine has not been identified.

Naftifine has been shown to be active against most isolates of the following fungi, both in vitroand in clinical infections, as described in the INDICATIONS AND USAGE section:

- Trichophyton rubrum

13 NONCLINICAL TOXICOLOGY

13.1 Carcinogenesis, Mutagenesis, Impairment of Fertility

In a 2-year dermal carcinogenicity study, naftifine hydrochloride cream was administered to Sprague-Dawley rats at topical doses of 1%, 2% and 3% (10 mg/kg/day, 20 mg/kg/day, and 30 mg/kg/day naftifine hydrochloride). No drug-related tumors were noted in this study up to the highest dose evaluated in this study of 30 mg/kg/day (12 times MRHD based on AUC comparison).

Naftifine hydrochloride revealed no evidence of mutagenic or clastogenic potential based on the results of two in vitrogenotoxicity tests (Ames assay and Chinese hamster ovary cell chromosome aberration assay) and one in vivogenotoxicity test (mouse bone marrow micronucleus assay).

Oral administration of naftifine hydrochloride to rats, throughout mating, gestation, parturition and lactation, demonstrated no effects on growth, fertility or reproduction, at doses up to 100 mg/kg/day (6 times MRHD based on mg/m^2comparison).

14 CLINICAL STUDIES

14.1 Tinea Cruris

Naftifine Hydrochloride Cream has been investigated for safety and efficacy in a randomized, double-blind, vehicle-controlled, multi-center trial in 146 subjects with symptomatic and dermatophyte culture positive tinea cruris. Subjects were randomized to receive Naftifine Hydrochloride Cream or vehicle. Subjects applied Naftifine Hydrochloride Cream or vehicle to the affected area plus a ½-inch margin of healthy skin surrounding the affected area once-daily for 2 weeks. Signs and symptoms of tinea cruris (presence or absence of erythema, pruritus, and scaling) were assessed, and KOH examination and dermatophyte culture were performed at the primary efficacy endpoint at week 4.

The mean age of the trial population was 47 years and 87% were male and 43% were white. At baseline, subjects were confirmed to have signs and symptoms of tinea cruris, positive KOH exam, and confirmed dermatophyte presence based on culture results from a central mycology laboratory. The analysis of the intent-to-treat population was a comparison of the proportions of subjects with a complete cure at the week 4 visit (see Table 1). Complete cure was defined as both clinical cure (absence of erythema, pruritus, and scaling) and mycological cure (negative KOH and dermatophyte culture).

The percentage of subjects experiencing clinical cure and the percentage of subjects experiencing mycological cure at week 4 are presented individually in Table 1 below.

Table 1 Efficacy Results for Tinea Cruris Trial (Week 4 Assessment)
Endpoint | Naftifine Hydrochloride Cream, 2% N=75 | Vehicle N=71
Complete Cure [Complete cure is a composite endpoint of both mycological cure and clinical cure. Clinical cure is defined as the absence of erythema, pruritus, and scaling (grade of 0).] | 19 (25%) | 2 (3%)
Effective Treatment [Effective treatment is a negative KOH preparation and negative dermatophyte culture, erythema, scaling, and pruritus grades of 0 or 1 (absent or nearly absent).] | 45 (60%) | 7 (10%)
Mycological Cure [Mycological cure is defined as negative KOH and dermatophyte culture.] | 54 (72%) | 11 (16%)

14.2 Interdigital Tinea Pedis

Naftifine Hydrochloride Cream has been investigated for efficacy in a randomized, double-blind, vehicle-controlled, multi-center trial in 217 subjects with symptomatic and dermatophyte culture positive interdigital tinea pedis. Subjects were randomized to receive Naftifine Hydrochloride Cream or vehicle. Subjects applied Naftifine Hydrochloride Cream or vehicle to the affected area of the foot plus a ½-inch margin of healthy skin surrounding the affected area once-daily for 2 weeks. Signs and symptoms of interdigital tinea pedis (presence or absence of erythema, pruritus, and scaling) were assessed and KOH examination and dermatophyte culture was performed at the primary efficacy endpoint at week 6.

The mean age of the trial population was 42 years and 71% were male and 57% were white. At baseline, subjects were confirmed to have signs and symptoms of interdigital tinea pedis, positive KOH exam, and confirmed dermatophyte culture. The primary efficacy endpoint was the proportions of subjects with a complete cure at the week 6 visit (see Table 2). Complete cure was defined as both a clinical cure (absence of erythema, pruritis, and scaling) and mycological cure (negative KOH and dermatophyte culture).

The efficacy results at week 6, four weeks following the end of treatment, are presented in Table 2 below. Naftifine Hydrochloride Cream demonstrated complete cure in subjects with interdigital tinea pedis, but complete cure in subjects with only moccasin type tinea pedis was not demonstrated.

Table 2 Efficacy Results for Interdigital Tinea Pedis Trial (Week 6 Assessment)
Endpoint | Naftifine Hydrochloride Cream, 2% N=147 | Vehicle N=70
Complete Cure [Complete cure is a composite endpoint of both mycological cure and clinical cure. Clinical cure is defined as absence of erythema, pruritus, and scaling (grade of 0).] | 26 (18%) | 5 (7%)
Effective Treatment [Effective treatment is a negative KOH preparation and negative dermatophyte culture, erythema, scaling, and pruritus grades of 0 or 1 (absent or near absent).] | 83 (57%) | 14 (20%)
Mycological Cure [Mycological cure is defined as negative KOH and dermatophyte culture.] | 99 (67%) | 15 (21%)

14.3 Tinea Corporis

Naftifine Hydochloride Cream has been investigated for safety and efficacy in a randomized, double-blind, vehicle-controlled, multi-center trial in 184 subjects with symptomatic and dermatophyte culture positive tinea corporis. Subjects were randomized to receive Naftifine Hydrochloride Cream or vehicle. Subjects applied the study agent to all affected body surface areas with tinea corporis plus a ½ inch margin of healthy skin surrounding the affected lesions for two weeks. Signs and symptoms of tinea corporis (presence or absence of erythema, induration, and pruritus) were assessed and KOH examination and dermatophyte culture were performed for the assessment of primary efficacy endpoint at Day 21.

The trial population was pediatric (≥2 to <18 years of age) with a median age of 9 years (Naftifine Hydrochloride Cream) or 8 years (vehicle); 61% of subjects were male and 45% were white. At baseline, subjects were confirmed to have signs and symptoms of tinea corporis, positive KOH exam, and confirmed dermatophyte culture. The primary efficacy endpoint was the proportions of subjects with a complete cure at the Day 21 visit. Complete cure was defined as both a clinical cure (absence of erythema, induration, and pruritus on all lesions present at baseline) and mycological cure (negative KOH and dermatophyte culture).

The efficacy results at Day 21, one week following the end of treatment, are presented in Table 3 below.

Table 3 Efficacy Results for Pediatric Tinea Corporis Trial (Day 21 Assessment)
Endpoint | Naftifine Hydrochloride Cream, 2% N=91 | Vehicle N=93
Complete Cure [Complete cure is a composite endpoint of both mycological cure and clinical cure. Clinical cure is defined as absence of erythema, pruritus, and scaling (grade of 0).] | 42 (46%) | 26 (28%)
Effective Treatment [Effective treatment is a negative KOH preparation and negative dermatophyte culture, erythema, induration, and pruritus grades of 0 or 1 (absent or mild).] | 53 (58%) | 32 (34%)
Mycological Cure [Mycological cure is defined as negative KOH and dermatophyte culture.] | 57 (63%) | 36 (39%)

16 HOW SUPPLIED/STORAGE AND HANDLING

How Supplied

Naftifine Hydrochloride Cream USP, 2% is a white to off-white cream supplied in tubes in the following sizes:

30 g – NDC 51672-1368-2
45 g – NDC 51672-1368-6
60 g – NDC 51672-1368-3

STORAGE AND HANDLING

Storage: Store Naftifine Hydrochloride Cream USP, 2% at 20° to 25°C (68° to 77°F)[see USP Controlled Room Temperature].

17 PATIENT COUNSELING INFORMATION

- Inform patients that Naftifine Hydrochloride Cream is for topical use only. Naftifine Hydrochloride Cream is not intended for oral, intravaginal or ophthalmic use.
- If irritation or sensitivity develops with the use of Naftifine Hydrochloride Cream treatment should be discontinued and appropriate therapy instituted. Patients should be directed to contact their physician if these conditions develop following use of Naftifine Hydrochloride Cream.

Manufactured by: Sun Pharma Canada Inc.
Brampton, Ontario, Canada L6T 1C1
Distributed by: Sun Pharmaceutical Industries, Inc.
Cranbury, NJ 08512

Revised: October 2025
5265017-1025-01
22

PRINCIPAL DISPLAY PANEL - 30 g Tube Carton

Naftifine Hydrochloride

Cream USP, 2%

FOR TOPICAL USE ONLY. NOT FOR OPHTHALMIC USE, ORAL OR INTRAVAGINAL USE

Rx only

Keep this and all medications out of the reach of children.